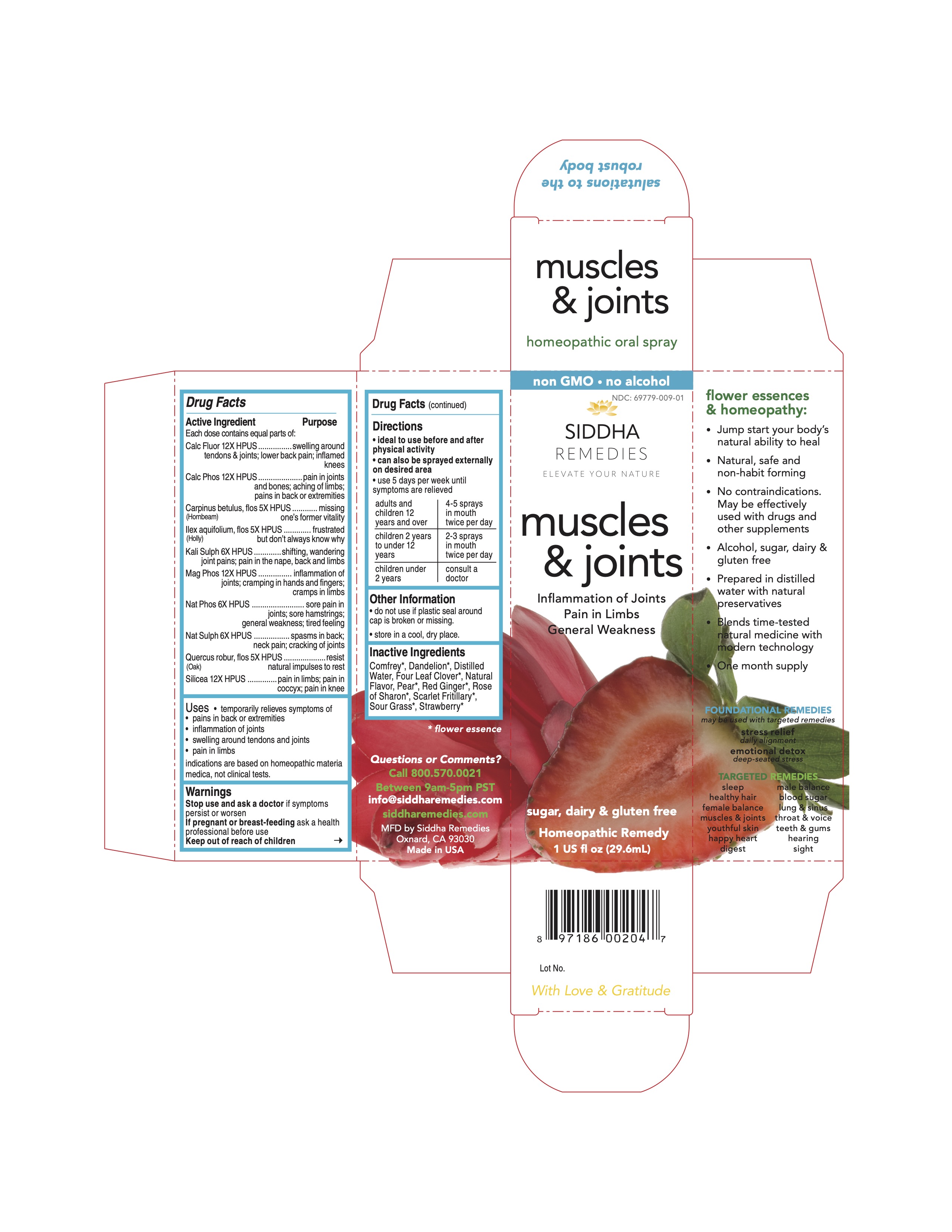 DRUG LABEL: muscles and joints
NDC: 69779-009 | Form: SPRAY
Manufacturer: Siddha Flower Essences LLC
Category: homeopathic | Type: HUMAN OTC DRUG LABEL
Date: 20251231

ACTIVE INGREDIENTS: CALCIUM FLUORIDE 12 [hp_X]/29.6 mL; TRIBASIC CALCIUM PHOSPHATE 12 [hp_X]/29.6 mL; CARPINUS BETULUS FLOWERING TOP 5 [hp_X]/29.6 mL; ILEX AQUIFOLIUM FLOWERING TOP 5 [hp_X]/29.6 mL; POTASSIUM SULFATE 6 [hp_X]/29.6 mL; MAGNESIUM PHOSPHATE, DIBASIC TRIHYDRATE 12 [hp_X]/29.6 mL; SODIUM PHOSPHATE, DIBASIC, HEPTAHYDRATE 6 [hp_X]/29.6 mL; SODIUM SULFATE 6 [hp_X]/29.6 mL; QUERCUS ROBUR FLOWER 5 [hp_X]/29.6 mL; SILICON DIOXIDE 12 [hp_X]/29.6 mL
INACTIVE INGREDIENTS: TARAXACUM OFFICINALE FLOWERING TOP; PEAR; WATER; STRAWBERRY

Drug Facts

Active Ingredient

1

Each dose contains equal parts of:

Calc Fluor 12X HPUS
Calc Phos 12X HPUS
Carpinus betulus, flos (Hornbeam) 5X HPUS
Ilex aquifolium, flos (Holly) 5X HPUS
Kali Sulph 6X HPUS
Mag Phos 12X HPUS
Nat Phos 6X HPUS
Nat Sulph 6X HPUS
Quercus robur, flos (Oak) 5X HPUS
Silicea 12X HPUS

Purpose

Each dose contains equal parts of:
Calc Fluor 12X HPUS............................................swelling around tendons and joints; lower back pain; inflamed knees
Calc Phos 12X HPUS..........................................pain in joints and bones; aching of limbs; pains in back or extremities
Carpinus betulus, flos (Hornbeam) 5X HPUS.........missing one's former vitality
Ilex aquifolium, flos (Holly) 5X HPUS....................frustrated but don't always know why
Kali Sulph 6X HPUS...........................................shifting, wandering joint pains; pain in the nape, back and limbs
Mag Phos 12X HPUS..........................................inflammation of joints; cramping in hands and fingers; cramps in limbs
Nat Phos 6X HPUS.............................................sore pain in joints; sore hamstrings; general weakness; tired feeling

Nat Sulph 6X HPUS............................................spasms in back; neck pain; cracking of joints

Quercus robur, flos (Oak) 5X HPUS......................resist natural impulses to rest
Silicea 12X HPUS...............................................pain in limbs; pain in coccyx; pain in knee

Uses

- temporarily relieves symptoms of
- pains in back or extremities
- inflammation of joints
- swelling around tendons and joints
- pain in limbs

indications are based on homeopathic materia medica, not clinical tests.

Warnings

Stop use and ask a doctor if symptoms persist or worsen

PREGNANCY OR BREAST FEEDING

If pregnant or breast-feeding ask a health professional before use

Keep out of reach of children

Directions

- ideal to use before and after physical activity
- can also be sprayed externally on desired area
- use 5 days per week until symptoms are relieved

adults and children 12 years and over | 4-5 sprays in mouth twice per day
children 2 years to under 12 years | 2-3 sprays in mouth twice per day
children under 2 years | consult a doctor

Other Information

- do not use if plastic seal around cap is broken or missing.
- store in a cool, dry place.

Inactive Ingredients

Comfrey*, Dandelion*, Four Leaf Clover*, Natural Flavor, Pear*, Purified Water, Red Ginger*, Rose of Sharon*, Scarlet Fritillary*, Sour Grass*, Strawberry*

*flower essence

Questions or Comments?
Call 800.570.0021
Between 9am-5pm PST
info@siddhaflowers.com
siddhaflowers.com

MFD by Siddha Flower Essences
Oxnard, CA 93030

Made in USA

Side Panel

flower essences and homeopathy:

- Jump start your body's natural ability to heal
- Natural, safe and non-habit forming
- No contraindications. May be effectively used with drugs and other supplements
- Alcohol, sugar, dairy and gluten free
- Prepared in purified water with natural preservatives
- Blends time-tested natural medicine with modern technology
- One month supply

FOUNDATIONAL REMEDIES
may be used with targeted remedies

stress relief
daily alignment
emotional detox
deep-seated stress

TARGETED REMEDIES

sleep male balance
healthy hair blood sugar
female balance lung and sinus
muscles and joints throat and voice
youthful skin teeth and gums
happy heart hearing
digestion sight

Principal Display Panel

non GMO - no alcohol
siddha cell salts + flower essences
muscles and joints
Inflammation of Joints
Pain in Limbs
General Weakness
sugar, dairy and gluten free
Homeopathic Remedy
1 US fl oz (29.6mL)